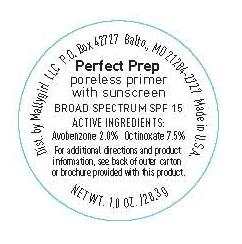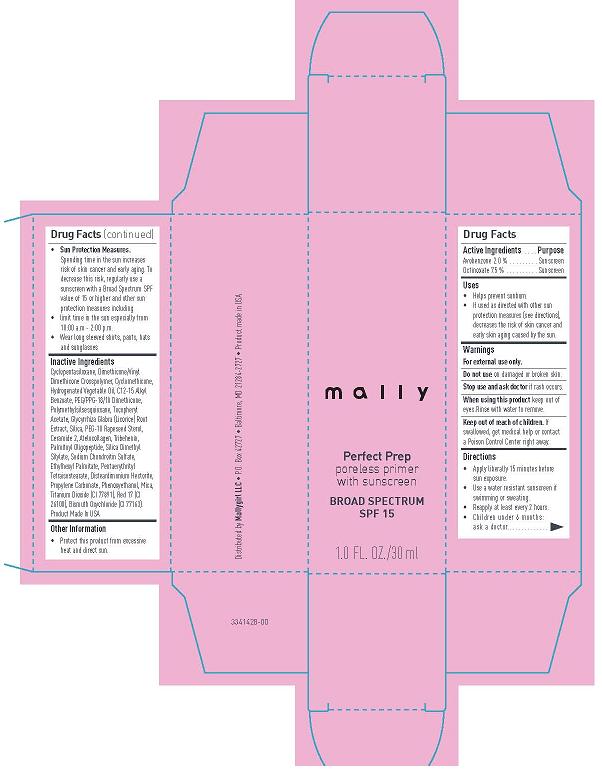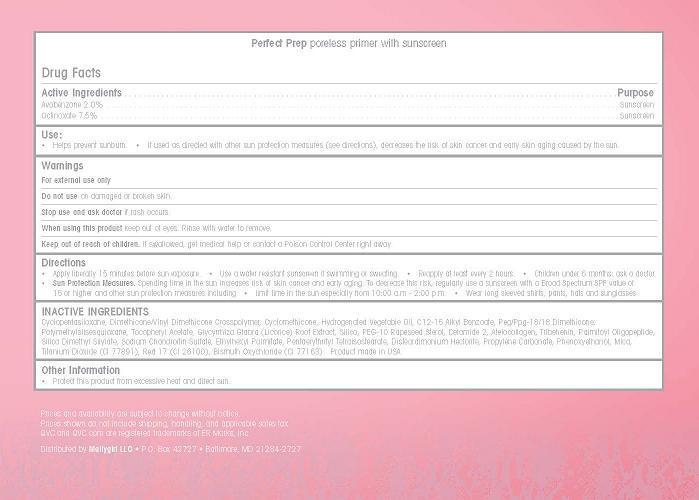 DRUG LABEL: mally Perfect Prep Poreless Primer
                
NDC: 76119-1170 | Form: CREAM
Manufacturer: MallyGirl, LLC
Category: otc | Type: HUMAN OTC DRUG LABEL
Date: 20130715

ACTIVE INGREDIENTS: AVOBENZONE 0.6 g/30.0 mL; OCTINOXATE 2.25 g/30.0 mL
INACTIVE INGREDIENTS: CYCLOMETHICONE 5; DIMETHICONE; CYCLOMETHICONE; CORN OIL; ALKYL (C12-15) BENZOATE; POLYETHYLENE GLYCOL 900; POLYMETHYLSILSESQUIOXANE (11 MICRONS); ALPHA-TOCOPHEROL ACETATE; GLYCYRRHIZA GLABRA; PEG-10 RAPESEED STEROL; CERAMIDE 2; TRIBEHENIN; PALMITOYL OLIGOPEPTIDE; SILICA DIMETHYL SILYLATE; SODIUM CHONDROITIN SULFATE (PORCINE; 5500 MW); PROPYLENE CARBONATE; PHENOXYETHANOL; MICA; TITANIUM DIOXIDE; D&C RED NO. 17; BISMUTH OXYCHLORIDE; SILICON DIOXIDE; PENTAERYTHRITYL TETRAISOSTEARATE; ETHYLHEXYL PALMITATE

mally Perfect Prep Poreless Primer Broad Spectrum SPF 15

Active Ingredients

Avobenzone 2.0%

Ocitnaxate 7.5%

Purpose

Sunscreen

Sunscreen

Use

- Helps prevent sunburn
- If used as directed with other sun protection measures (see directions), decreases the risk of skin cancer and early skin aging caused by the sun.

WARNINGS

For external use only

Do not use on damaged or broken skin.

Stop use and ask doctor if rash occurs.

When using this product keep out of eyes. Rinse with water to remove.

Keep out of reach of children. If swollowed, get medical help or contact a Poison Control Center right away.

Directions

- Apply liberally 15 minutes before sun exposure
- Use a water resistant sunscreen if swimming or sweating
- Reapply at least every 2 hours
- Children under 6 months: ask a doctor
- Sun Protection Measures. Spending time in the sun increases risk of skin cancer and early aging. To decrease this risk regularly use a sunscreen with a Broad Spectrum SPF value of 15 or higer and other sun protection measures including
- Limit time in the sun especially from 10:00 a.m. - 2:00 p.m.
- Wear long sleeved shirts, pants, hats and sunglasses

Inactive Ingredients

Cyclopentasiloxane, Dimethicone/Vinyl Dimeticone Crosspolymer, Cyclomethicone, Hydrogenated Vegetable Oil, C12-15 Alkyl Benzoate, Peg/Ppg-18/18 Dimethicone, Polymethylsilsesquioxane, Tocopheryl Acetate, Glycyrrhiza Glabra (Licorice) Root Extract, Silica, PEG-10 Rapeseed Sterol, Ceramide 2, Atelocollagen, Tribehenin, Palmitoyl Oligopeptide, Silica Dimethyl Silylate, Sodium Chondroitin Sulfate, Pentaerythrityl Tetraisostearate, Ethylthexyl Palmitate, Disteardimonium Hectorite, Propylene Carbonate, Phenoxyethanol, Mica, Titanium Dioxide (CI 77891), Red 17 (CI 26100), Bismuth Oxychloride (CI 77163). Product made in the USA

Other Information

- Protect this product from excessive heat and direct sun.

Prices and availability are subject to change without notice.

Prices shown do not include shipping, handling, and applicable sales tax.

QVC and QVC.com are registered trademarks of ER Marks, Inc.

Distributed by Mallygirl LLC - P.O. Box 42727 - Baltimore, MD 21284-2727

Principal Display Panel

mally

Perfect Prep

Poreless Primer

with sunscreen

Broad Spectrum

SPF15